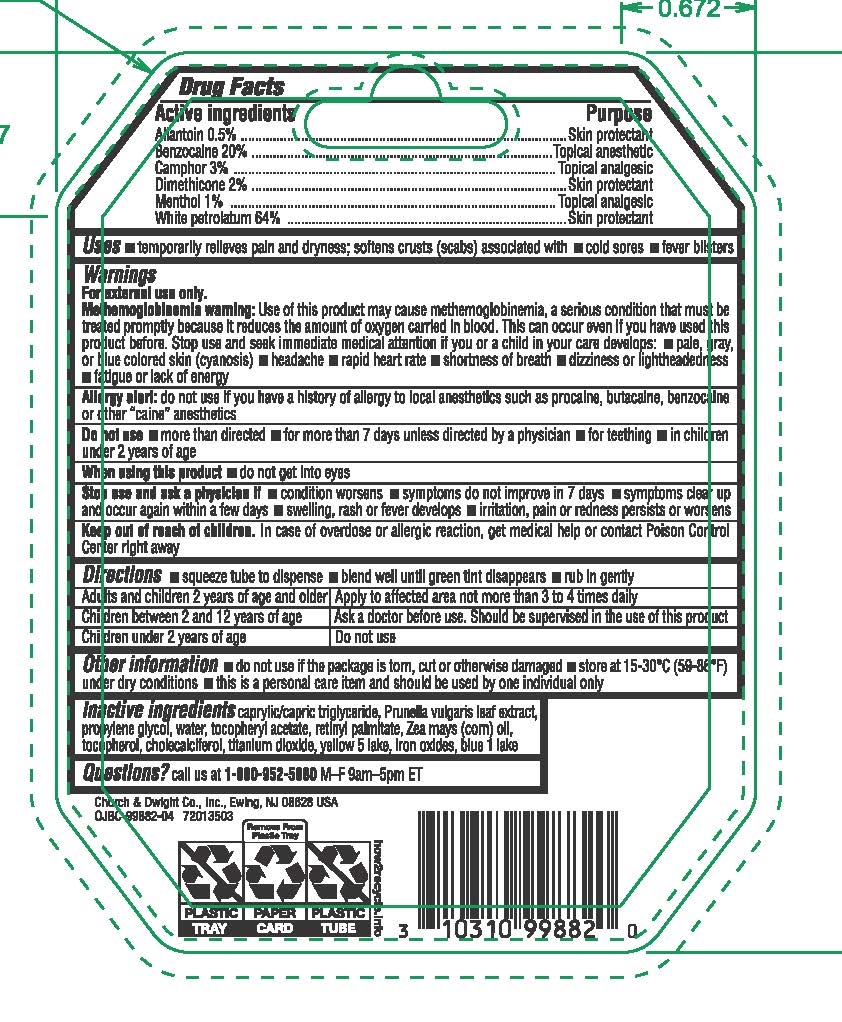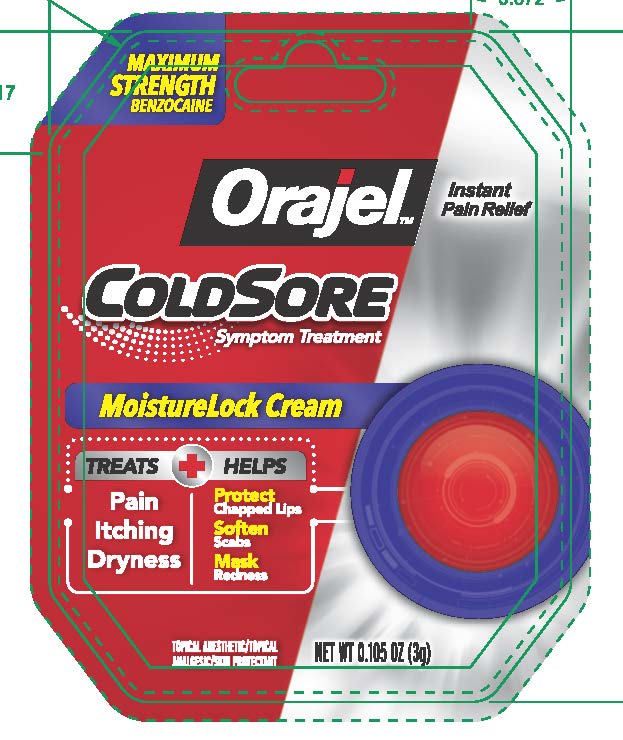 DRUG LABEL: Orajel Cold Sore Moisturelock
NDC: 10237-761 | Form: CREAM
Manufacturer: Church & Dwight Co., Inc.
Category: otc | Type: HUMAN OTC DRUG LABEL
Date: 20241126

ACTIVE INGREDIENTS: BENZOCAINE 200 mg/1 g; ALLANTOIN 5 mg/1 g; CAMPHOR (NATURAL) 30 mg/1 g; DIMETHICONE 20 mg/1 g; MENTHOL 10 mg/1 g; PETROLATUM 640 mg/1 g
INACTIVE INGREDIENTS: MEDIUM-CHAIN TRIGLYCERIDES; PRUNELLA VULGARIS LEAF; TITANIUM DIOXIDE; FD&C YELLOW NO. 5; PROPYLENE GLYCOL; .ALPHA.-TOCOPHEROL ACETATE; VITAMIN A PALMITATE; CORN OIL; CHOLECALCIFEROL; FERRIC OXIDE RED; FD&C BLUE NO. 1; TOCOPHEROL

Orajel Cold Sore Moisturelock

ACTIVE INGREDIENT

Allantoin 0.5%

Benzocaine 20%

Camphor 3%

Dimethicone 2%

Menthol 1%

White petrolatum 64%

PURPOSE

Allantoin - Skin protectant

Benzocaine - Topical anesthetic

Camphor - Topical analgesic

Dimethicone - Skin protectant

Menthol - Topical analgesic

White petrolatum - Skin protectant

INDICATIONS AND USAGE

Uses •temporarily relieves pain and dryness; softens crusts (scabs) associated with • cold sores • fever blisters

WARNINGS

For external use only.

Allergy alert:do not use if you have a history of allergy to local anesthetics such as procaine, butacaine, benzocaine or other "caine" anesthetics

Do not use •more than directed • for more than 7 days unless directed by a physician

When using this product• do not get into eyes

Stop use and ask a physician if• conditions worsens • symptoms do not improve in 7 days • symptoms clear up and occur again within a few days • swelling, rash or fever develops • irritation, pain or redness persists or worsens

Keep out of reach of children.In case of overdose or allergic reaction, get medical help or contact Poison Control Center right away.

Directions

• squeeze tube to dispense • blend well until green tint disappears • rub in gently

Adults and children 2 years of age and older | Apply to affected area not more than 3 to 4 times daily

Children under 12 years of age | Should be supervised in the use of this product

Children under 2 years of age | Ask a physician

Other information • do not use if the package is torn, cut or otherwise damaged • store at 15-30ºC (59-86º) under dry conditions • this is a personal care item and should be used by one individual only

INACTIVE INGREDIENT

Inactive Ingredientscaprylic/capric triglyceride, Prunella vulgaris leaf extract. propylene glycol, water, tocopheryl acetate, retinyl palmitate, Zea mays (corn) oil, tocopherol, cholecalciferol, titanium dioxide, yellow 5 lake, iron oxides, blue 1 lake

QUESTIONS

Questions or commentscall us at 800 952 5080 Monday through Friday 9 to 5 ET or visit www orajel com

PACKAGE LABEL

Orajel

Instan Pain Relief

FOR COLD SORES

MOISTURELOCK FORMULA

Helps Speed Healing

Treats 6 Symptoms:

1 Pain

2 Itching

3 Redness

4 Scabbing

5 Cracking

6 Dryness

PLUS

Helps Minimize Appearance of Cold Sores

Topical Anesthetic/Topical

Analgesic/Skin Protectant

NET WT 0.105 OZ (3g)